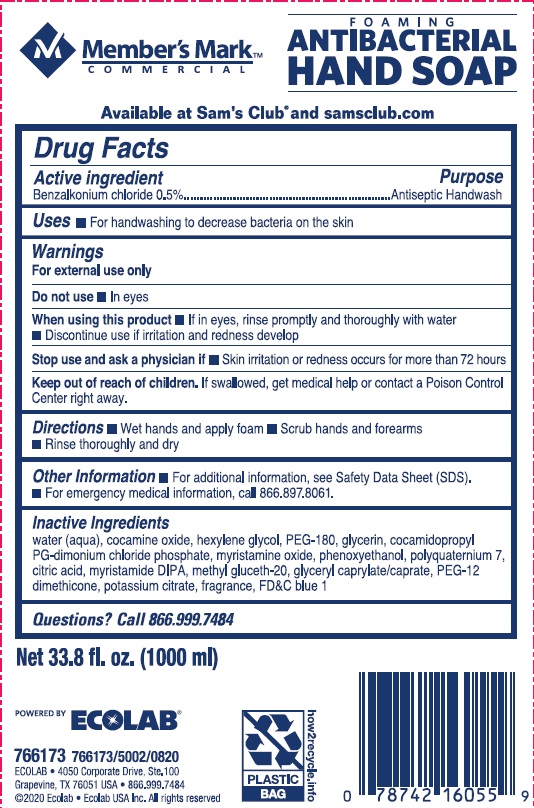 DRUG LABEL: Members Mark
NDC: 47593-572 | Form: SOLUTION
Manufacturer: Ecolab Inc.
Category: otc | Type: HUMAN OTC DRUG LABEL
Date: 20240802

ACTIVE INGREDIENTS: BENZALKONIUM CHLORIDE 5 mg/1 mL
INACTIVE INGREDIENTS: FD&C BLUE NO. 1; POTASSIUM CITRATE; PEG-12 DIMETHICONE (300 CST); GLYCERYL MONO- AND DICAPRYLOCAPRATE; METHYL GLUCETH-20; MYRISTIC DIISOPROPANOLAMIDE; ANHYDROUS CITRIC ACID; POLYQUATERNIUM-7 (70/30 ACRYLAMIDE/DADMAC; 1600000 MW); PHENOXYETHANOL; MYRISTAMINE OXIDE; COCAMIDOPROPYL PG-DIMONIUM CHLORIDE PHOSPHATE; GLYCERIN; POLYETHYLENE GLYCOL 8000; HEXYLENE GLYCOL; WATER; COCAMINE OXIDE

Drug Facts

Active Ingredient

Benzalkonium chloride 0.5%

Purpose

Antiseptic handwash

Uses

- for handwashing to decrease bacteria on the skin

Warning

For external use only

Do not use

- in eyes

When using the product

- if in eyes, rinse promptly and thoroughly with water
- discontinue use if irritation and redness develop

Stop use and ask a physician if

- Skin irritation or redness occurs for more than 72 hours

Keep out of reach of children. If swallowed, get medical help or contact a Poison Control Center right away.

Directions

- wet hands and apply foam
- scrub hands and forearms
- rinse thoroughly and dry

Other information

- for additional information, see Safety Data Sheet (SDS)
- for emergency medical information, call 866.897.8061

INACTIVE INGREDIENT

Inactive ingredients water (aqua), cocamine oxide, hexylene glycol, PEG-180, glycerin, cocamidopropyl PG-dimonium chloride phosphate, myristamine oxide, phenoxyethanol, polyquaternium 7, citric acid, myristamide DIPA, methyl gluceth-20, glyceryl caprylate/caprate, PEG-12 dimethicone, potassium citrate, fragrance, FD&C blue 1

Questions? call 866.999.7484

Representative Label and Principal Display Panel

Member's Mark

COMMERCIAL

FOAMING

ANTIBACTERIAL

HAND SOAP

Available at Sam's Club and samsclub.com

Net 33.8 fl. oz. (1000 ml)

766173-00 766173/5002/0820

ECOLAB • 4050 Corporate Drive STE 100

Grapevine, TX 76051

© 2020 Ecolab • Ecolab USA Inc., All rights reserved.